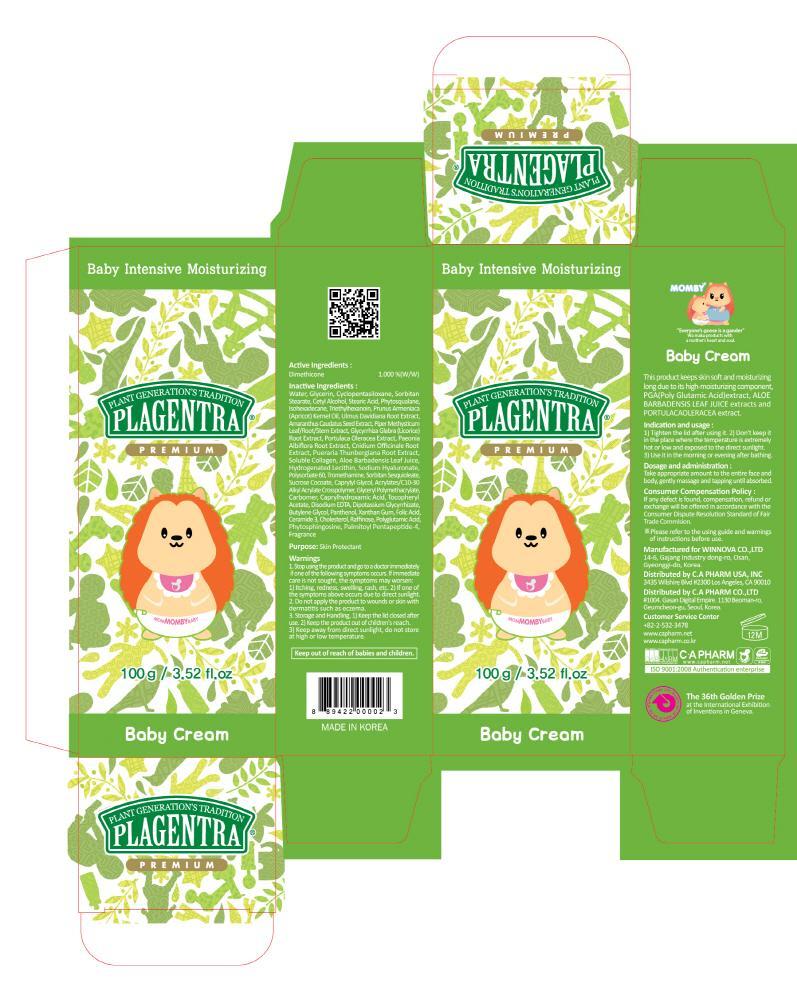 DRUG LABEL: PLAGENTRA BABY
NDC: 68988-060 | Form: CREAM
Manufacturer: C.A Pharm Co., Ltd.
Category: otc | Type: HUMAN OTC DRUG LABEL
Date: 20141208

ACTIVE INGREDIENTS: Dimethicone 1 g/100 g
INACTIVE INGREDIENTS: Water; Glycerin

ACTIVE INGREDIENT

Active Ingredient: Dimethicone 1%

INACTIVE INGREDIENT

Inactive Ingredients:
Water, Glycerin, Cyclopentasiloxane, Sorbitan Stearate, Cetyl Alcohol, Stearic Acid, Phytosqualane, Isohexadecane, Triethylhexanoin, Prunus Armeniaca (Apricot) Kernel Oil, Ulmus Davidiana Root Extract, Amaranthus Caudatus Seed Extract, Piper Methysticum Leaf/Root/Stem Extract, Glycyrrhiza Glabra (Licorice) Root Extract, Portulaca Oleracea Extract, Paeonia Albiflora Root Extract, Cnidium Officinale Root Extract, Pueraria Thunbergiana Root Extract, Soluble Collagen, Aloe Barbadensis Leaf Juice, Hydrogenated Lecithin, Sodium Hyaluronate, Polysorbate 60, Tromethamine, Sorbitan Sesquioleate, Sucrose Cocoate, Caprylyl Glycol, Acrylates/C10-30 Alkyl Acrylate Crosspolymer, Glyceryl Polymethacrylate, Carbomer, Caprylhydroxamic Acid, Tocopheryl Acetate, Disodium EDTA, Dipotassium Glycyrrhizate, Butylene Glycol, Panthenol, Xanthan Gum, Folic Acid, Ceramide 3, Cholesterol, Raffinose, Polyglutamic Acid, Phytosphingosine, Palmitoyl Pentapeptide-4, Fragrance

PURPOSE

Purpose: Skin Portectant

WARNINGS

1. Stop using the product and go to a doctor immediately if one of the following symptoms occurs. If immediate care is not sought, the symptoms may worsen :
1) Itching, redness, swelling, rash, etc. 2) If one of the symptoms above occurs due to direct sunlight.
2. Do not apply the product to wounds or skin with dermatitis such as eczema.
3. Storage and Handling, 1) Keep the lid closed after use. 2) Keep the product out of children's reach. 3) Keep away from direct sunlight, do not store at high or low temperature.

KEEP OUT OF REACH OF CHILDREN

Keep out of reach of babies and children.

INDICATIONS & USAGE

Indication and usage:
1) Tighten the lid after using it.
2) Don't keep it in the place where the temperature is extremely hot or low and exposed to the direct sunlight.
3) Use it in the morning or evening after shower.

DOSAGE & ADMINISTRATION

Dosage and administration:
Take appropriate amount to the entire face and body, gently massage and tapping until absorbed.